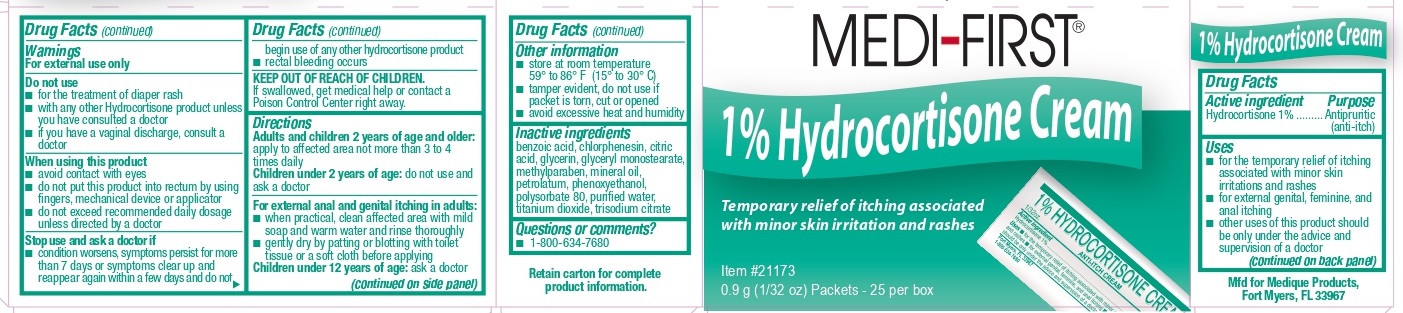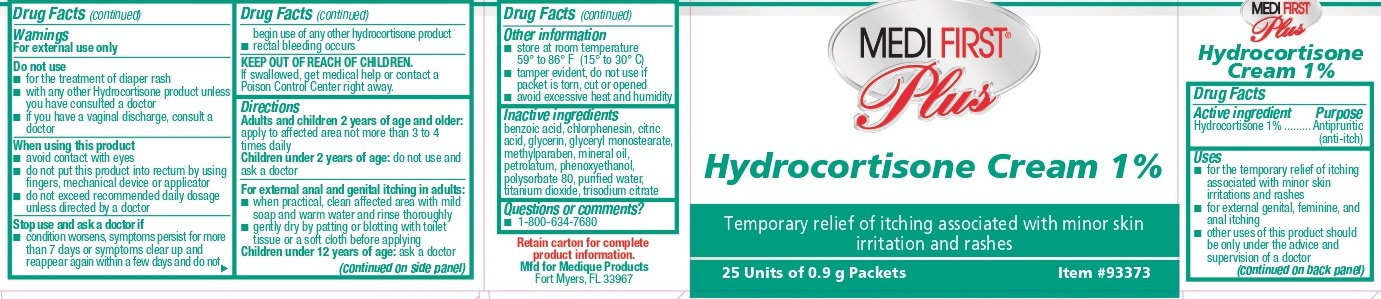 DRUG LABEL: Medi-First Plus Hydrocortisone
NDC: 47682-633 | Form: CREAM
Manufacturer: Unifirst First Aid Corporation
Category: otc | Type: HUMAN OTC DRUG LABEL
Date: 20230810

ACTIVE INGREDIENTS: HYDROCORTISONE 10 mg/1 g
INACTIVE INGREDIENTS: METHYLPARABEN; PHENOXYETHANOL; POLYSORBATE 80; TITANIUM DIOXIDE; TRISODIUM CITRATE DIHYDRATE; BENZOIC ACID; CITRIC ACID MONOHYDRATE; PETROLATUM; WATER; MINERAL OIL; GLYCERYL MONOSTEARATE; CHLORPHENESIN; GLYCERIN

Medi-First 1% Hydrocortisone Cream

Active ingredient

Hydrocortisone 1.0%

Purpose

Antipruritic (ant-itch)

Uses

- for the temporary relief of itching associated with minor skin irritations, inflammation and rashes
- for external genital, feminine, and anal itching
- other uses of this product should be only under the advice and supervision of a doctor

Warnings

For external use only.

Do not use

- for the treatment of diaper rash
- with any other Hydrocortisone product unless you have consulted a doctor
- if you have a vaginal discharge, consult a doctor

When using this product

- avoid contact with eyes
- do not put this product into rectum by using fingers, mechanical device or applicator
- do not exceed recommended daily dosage unless directed by a doctor

Stop use and ask a doctor if

- condition worsens, symptoms persist for more than 7 days or symptoms clear up and reappear again within a few days and do not begin use of any other hydrocortisone product
- rectal bleeding occurs

KEEP OUT OF REACH OF CHILDREN.

If swallowed, get medical help or contact a Poison Control Center right away.

Directions

Adults and children 2 years of age and older: apply to affected area not more than 3 to

4 times daily

Children under 2 years of age: do not use and ask a doctor

For external anal and genital itching in adults:

- when practical, clean affected area with mild soap and warm water and rinse thoroughly
- gently dry by patting or blotting with toilet tissue or a soft cloth before applying

Children under 12 years of age: ask a doctor

Other information

- store at room temperature 59° to 86° F (15° to 30° C)
- tamper evident, do not use if packet is torn, cut or opened
- avoid excessive heat and humidity

Inactive ingredients

benzoic acid, chlorphenesin, citric acid, glycerin, glyceryl monostearate, methylparaben, mineral oil, petrolatum, phenoxyethanol, polysorbate 80, purified water, titanium dioxide, trisodium citrate

Questions or comments?

1-800-634-7680

Medi-First 1% Hydrocortisone Cream Label

Medi-First®

1% Hydrocortisone Cream

Temporary relief of itching associated with minor skin irritation and rashes

Item # 21173

0.9g (1/32oz) Packets

25 per box

Medi-First Plus 1% Hydrocortisone Cream Label

Medi-First® Plus

Hydrocortisone Cream 1%

Temporary relief of itching associated with minor skin irritation and rashes

25 Units of 0.9g (1/32oz) Packets

Item # 93373